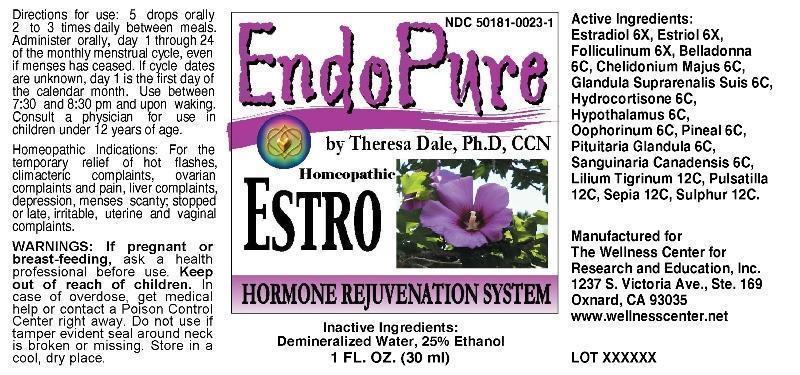 DRUG LABEL: EndoPure Estro
NDC: 50181-0023 | Form: LIQUID
Manufacturer: The Wellness Center for Research and Education
Category: homeopathic | Type: HUMAN OTC DRUG LABEL
Date: 20250529

ACTIVE INGREDIENTS: ESTRIOL 6 [hp_X]/1 mL; ESTRADIOL 6 [hp_X]/1 mL; ESTRONE 6 [hp_X]/1 mL; ATROPA BELLADONNA WHOLE 6 [hp_C]/1 mL; CHELIDONIUM MAJUS 6 [hp_C]/1 mL; HYDROCORTISONE 6 [hp_C]/1 mL; SUS SCROFA ADRENAL GLAND 6 [hp_C]/1 mL; SUS SCROFA HYPOTHALAMUS 6 [hp_C]/1 mL; SUS SCROFA OVARY 6 [hp_C]/1 mL; SUS SCROFA PINEAL GLAND 6 [hp_C]/1 mL; SUS SCROFA PITUITARY GLAND, POSTERIOR 6 [hp_C]/1 mL; SANGUINARIA CANADENSIS ROOT 6 [hp_C]/1 mL; LILIUM LANCIFOLIUM WHOLE FLOWERING 12 [hp_C]/1 mL; PULSATILLA VULGARIS 12 [hp_C]/1 mL; SEPIA OFFICINALIS JUICE 12 [hp_C]/1 mL; SULFUR 12 [hp_C]/1 mL
INACTIVE INGREDIENTS: WATER; ALCOHOL

DRUG FACTS:

ACTIVE INGREDIENTS:

Estriol 6X, Estradiol 6X, Folliculinum 6X, Belladonna 6C, Chelidonium Majus 6C, Cortisol (Hydrocortisone) 6C, Glandula Suprarenalis Suis 6C, Hypothalamus (Suis) 6C, Oophorinum (Suis) 6C, Pineal (Suis) 6C, Pituitary (Suis) 6C, Sanguinaria Canadensis 6C, Lilium Tigrinum 12C, Pulsatilla 12C, Sepia 12C, Sulphur 12C

INDICATIONS:

For the temporary relief of hot flashes, climacteric complaints, ovarian complaints and pain, liver complaints, depression, menses scanty; stopped or late, irritable, uterine and vaginal complaints.

WARNINGS:

If pregnant or breast-feeding, ask a health professional before use. Keep out of reach of children. In case of overdose, get medical help or contact a Poison Control Center right away. Do not use if tamper evident seal around neck is broken or missing. Store in a cool, dry place.

DIRECTIONS FOR USE:

5 drops orally 2 to 3 times daily between meals. Administer orally, day 1 through 24 of the monthly menstrual cycle, even if menses has ceased. If cycle dates are unknown, day 1 is the first day of the calendar month. Use between 7:30 and 8:30 pm and upon waking. Consult a physician for use in children under 12 years of age.

INACTIVE INGREDIENTS

Demineralized Water, Ethanol 25%

Keep out of reach of children. In case of overdose, get medical help or contact a Poison Control Center right away.

INDICATIONS AND USAGE:

For the temporary relief of hot flashes, climacteric complaints, ovarian complaints and pain, liver complaints, depression, menses scanty; stopped or late, irritable, uterine and vaginal complaints.

QUESTIONS:

Manufactured for

The Wellness Center for

Research and Education, Inc.

1237 S. Victoria Ave., Ste. 169

Oxnard, CA 93035

www.wellnesscenter.net

PACKAGE LABEL DISPLAY:

NDC 50181-0023-1

EndoPure

by Theresa Dale, Ph.D, CCN

Homeopathic

ESTRO

HORMONE REJUVENATION SYSTEM

1 FL OZ (30 ml)